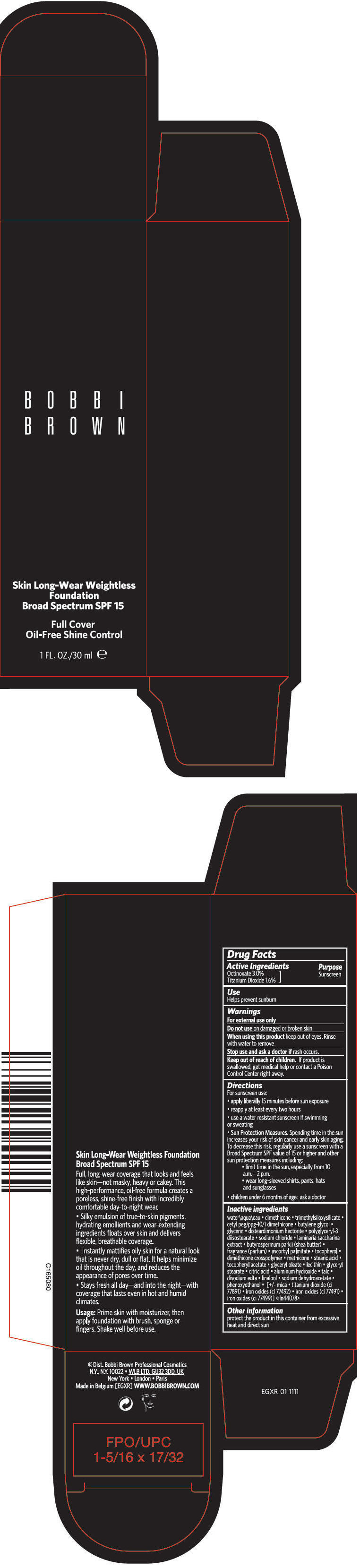 DRUG LABEL: SKIN LONG-WEAR WEIGHTLESS FOUNDATION BROAD SPECTRUM SPF 15
NDC: 64141-025 | Form: LOTION
Manufacturer: Bobbi Brown Professional Cosmetics Inc.
Category: otc | Type: HUMAN OTC DRUG LABEL
Date: 20241125

ACTIVE INGREDIENTS: OCTINOXATE 30 mg/1 mL; TITANIUM DIOXIDE 16 mg/1 mL
INACTIVE INGREDIENTS: WATER; DIMETHICONE; BUTYLENE GLYCOL; GLYCERIN; DISTEARDIMONIUM HECTORITE; POLYGLYCERYL-3 DIISOSTEARATE; SODIUM CHLORIDE; SACCHARINA LATISSIMA; SHEA BUTTER; ASCORBYL PALMITATE; TOCOPHEROL; DIMETHICONE CROSSPOLYMER (450000 MPA.S AT 12% IN CYCLOPENTASILOXANE); METHICONE (20 CST); STEARIC ACID; .ALPHA.-TOCOPHEROL ACETATE; GLYCERYL OLEATE; GLYCERYL MONOSTEARATE; CITRIC ACID MONOHYDRATE; ALUMINUM HYDROXIDE; TALC; EDETATE DISODIUM ANHYDROUS; LINALOOL, (+/-)-; SODIUM DEHYDROACETATE; PHENOXYETHANOL; MICA; FERRIC OXIDE YELLOW; FERRIC OXIDE RED; FERROSOFERRIC OXIDE

SKIN LONG-WEAR WEIGHTLESS FOUNDATION BROAD SPECTRUM SPF 15

Drug Facts

Active Ingredients

Octinoxate 3.0%
Titanium Dioxide 1.6%

Purpose

Sunscreen

Use

Helps prevent sunburn

Warnings

For external use only

Do not use on damaged or broken skin

When using this product keep out of eyes. Rinse with water to remove.

Stop use and ask a doctor if rash occurs.

Keep out of reach of children. If product is swallowed, get medical help or contact a Poison Control Center right away.

Directions

For suncreen use:

- apply liberally 15 minutes before sun exposure
- reapply at least every two hours
- use a water resistant sunscreen if swimming or sweating
- Sun Protection Measures. Spending time in the sun increases your risk of skin cancer and early skin aging. To decrease this risk, regularly use a suncreen with a Broad Spectrum SPF value of 15 or higher and other sun protection measures including:
  - limit time in the sun, especially from 10 a.m. – 2 p.m.
  - wear long-sleeved shirts, pants, hats and sunglasses
- children under 6 months of age: ask a doctor

Inactive ingredients

water\aqua\eau • dimethicone • trimethylsiloxysilicate • cetyl peg/ppg-10/1 dimethicone • butylene glycol • glycerin • disteardimonium hectorite • polyglyceryl-3 diisostearate • sodium chloride • laminaria saccharina extract • butyrospermum parkii (shea butter) • fragrance (parfum) • ascorbyl palmitate • tocopherol • dimethicone crosspolymer • methicone • stearic acid • tocopheryl acetate • glyceryl oleate • lecithin • glyceryl stearate • citric acid • aluminum hydroxide • talc • disodium edta • linalool • sodium dehydroacetate • phenoxyethanol • [+/- mica • titanium dioxide (ci 77891) • iron oxides (ci 77492) • iron oxides (ci 77491) • iron oxides (ci 77499)] <iln44078>

Other information

protect the product in this container from excessive heat and direct sun

PRINCIPAL DISPLAY PANEL - 30 ml Bottle Carton

BOBBI
BROWN

Skin Long-Wear Weightless
Foundation
Broad Spectrum SPF 15

Full Cover
Oil-Free Shine Control

1 FL. OZ./30 ml e